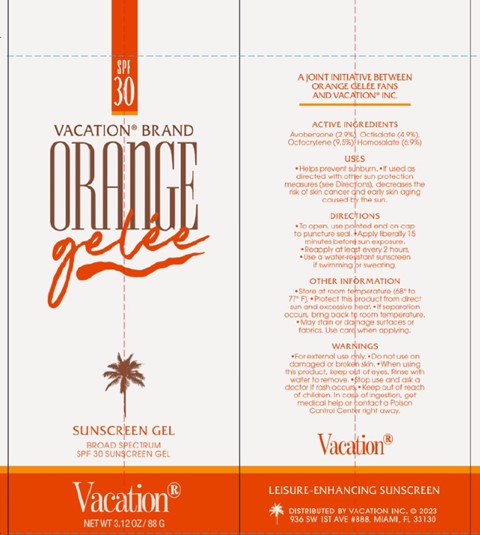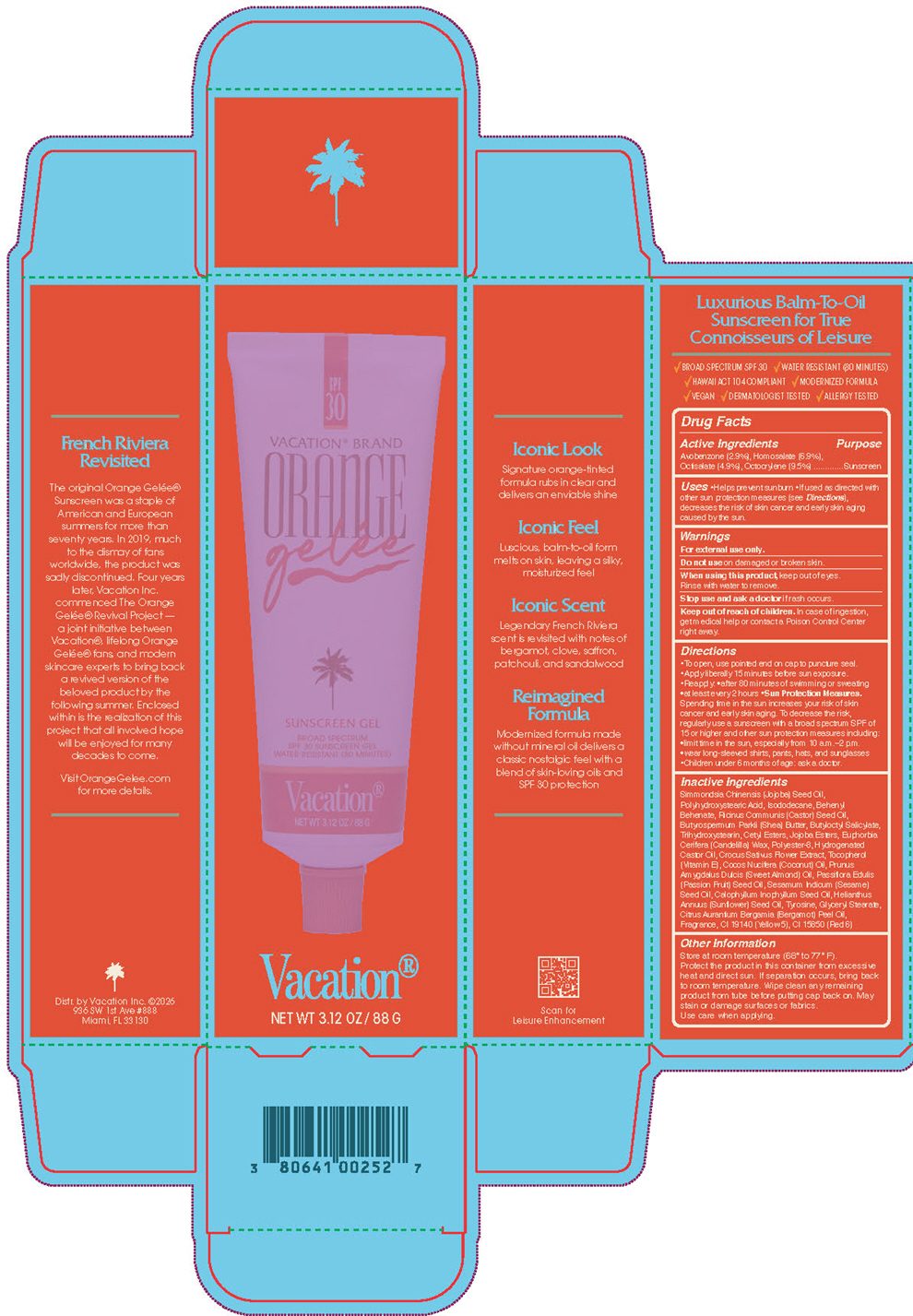 DRUG LABEL: Orange Gel
NDC: 80641-016 | Form: GEL
Manufacturer: Vacation Inc.
Category: otc | Type: HUMAN OTC DRUG LABEL
Date: 20260128

ACTIVE INGREDIENTS: AVOBENZONE 2.9 g/100 g; HOMOSALATE 6.9 g/100 g; OCTISALATE 4.9 g/100 g; OCTOCRYLENE 9.5 g/100 g
INACTIVE INGREDIENTS: BUTYLOCTYL SALICYLATE

Vacation® Orange Gelee

Dosage and Administration

Apply liberally 15 minutes before sun exposure

Reapply at least every 2 hours

Use a water resistant sunscreen if swimming or sweating

Warnings

For external use only

Do not use on damaged or broken skin

When using this product, keep out of eyes. Rinse with water to remove.

Stop use and ask a doctor if rash occurs

Indications and Usage

Helps prevent sunburn

If used as directed with other sun protection measures (see Directions), decreases the risk of skin cancer and early skin aging caused by the sun

Keep out of reach of children

In case of ingestion, get medical help or contact a Poison Control Center right away

Purpose

Sunscreen

Inactives

Behenyl Behenate, Butyloctyl Salicylate, Butyrospermum Parkii (Shea) Butter, Calophyllum Inophyllum Seed Oil, Cetyl Esters, Citrus Aurantium Bergamia (Bergamot) Peel Oil, Cocos Nucifera (Coconut) Oil, Crocus Sativus Flower Extract, Euphorbia Cerifera (Candelilla) Wax, Fragrance, Glyceryl Stearate, Helianthus Annuus (Sunflower) Seed Oil, Hydrogenated Castor Oil, Isododecane

PRINCIPAL DISPLAY PANEL - 88 G Tube Carton

SPF
30

VACATION® BRAND

ORANGE
gelee

SUNSCREEN GEL

BROAD SPECTRUM
SPF 30 SUNSCREEN GEL
WATER RESISTANT (80 MINUTES)

Vacation®

NET WT 3.12 OZ / 88 G